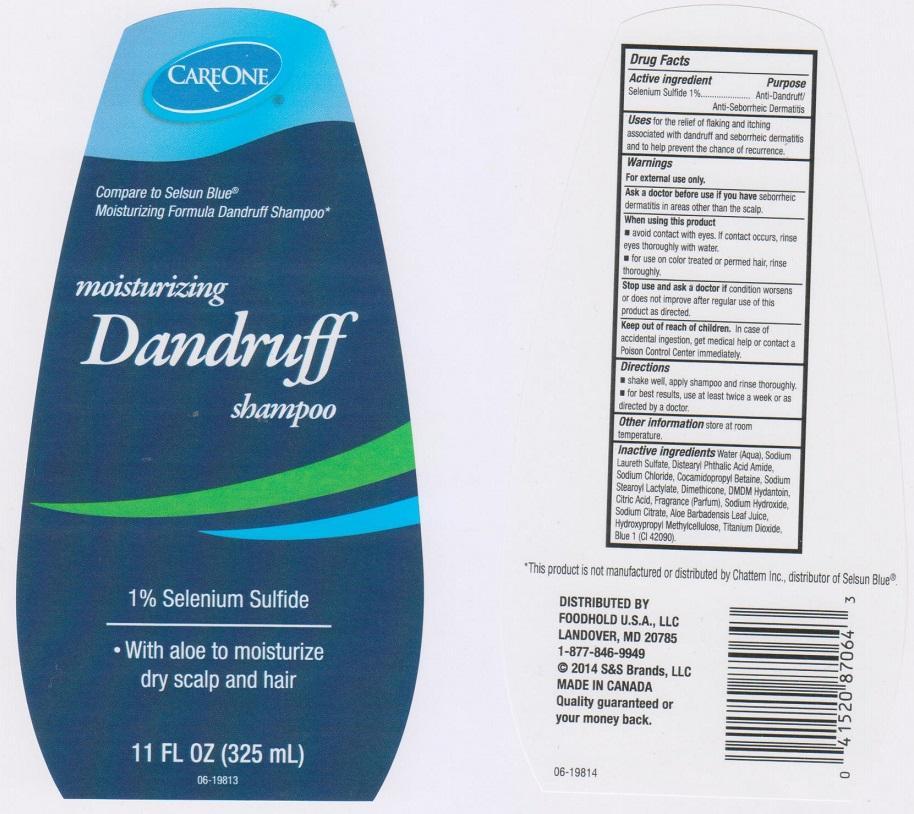 DRUG LABEL: CAREONE
NDC: 41520-622 | Form: LIQUID
Manufacturer: AMERICAN SALES COMPANY
Category: otc | Type: HUMAN OTC DRUG LABEL
Date: 20150114

ACTIVE INGREDIENTS: SELENIUM SULFIDE 10 mg/1 mL
INACTIVE INGREDIENTS: WATER; SODIUM LAURETH SULFATE; DISTEARYL PHTHALAMIC ACID; SODIUM CHLORIDE; COCAMIDOPROPYL BETAINE; SODIUM STEAROYL LACTYLATE; DIMETHICONE; DMDM HYDANTOIN; CITRIC ACID MONOHYDRATE; SODIUM HYDROXIDE; SODIUM CITRATE; ALOE VERA LEAF; HYPROMELLOSES; TITANIUM DIOXIDE; FD&C BLUE NO. 1

DRUG FACTS

ACTIVE INGREDIENT

SELENIUM SULFIDE 1%

PURPOSE

ANTI-DANDRUFF/ANTI-SEBORRHEIC DERMATITIS

USES

FOR THE RELIEF OF FLAKING AND ITCHING ASSOCIATED WITH DANDRUFF AND SEBORRHEIC DERMATITIS AND TO HELP PREVENT THE CHANCE OF RECURRENCE

WARNINGS

FOR EXTERNAL USE ONLY

ASK A DOCTOR BEFORE USE IF YOU HAVE

SEBORRHEIC DERMATITIS IN AREAS OTHER THAN THE SCALP

WHEN USING THIS PRODUCT

- AVOID CONTACT WITH EYES. IF CONTACT OCCURS, RINSE EYES THOROUGHLY WITH WATER
- FOR USE ON COLOR TREATED OR PERMED HAIR, RINSE THOROUGHLY

STOP USE AND ASK A DOCTOR IF

CONDITION WORSENS OR DOES NOT IMPROVE AFTER REGULAR USE OF THIS PRODUCT AS DIRECTED

KEEP OUT OF REACH OF CHILDREN

IN CASE OF ACCIDENTAL INGESTION, GET MEDICAL HELP OR CONTACT A POISON CONTROL CENTER IMMEDIATELY

DIRECTIONS

- SHAKE WELL, APPLY SHAMPOO AND RINSE THOROUGHLY
- FOR BEST RESULTS, USE AT LEAST TWICE A WEEK OR AS DIRECTED BY A DOCTOR

OTHER INFORMATION

STORE AT ROOM TEMPERATURE

INACTIVE INGREDIENTS

WATER (AQUA), SODIUM LAURETH SULFATE, DISTEARYL PHTHALIC ACID AMIDE, SODIUM CHLORIDE, COCAMDIOPROPYL BETAINE, SODIUM STEAROYL LACTYLATE, DIMETHICONE, DMDM HYDANTOIN, CITRIC ACID, FRAGRANCE (PARFUM), SODIUM HYDROXIDE, SODIUM CITRATE, ALOE BARBADENSIS LEAF JUICE, HYDROXYPROPYL METHYLCELLULOSE, TITANIUM DIOXIDE, BLUE 1 (CI 42090)